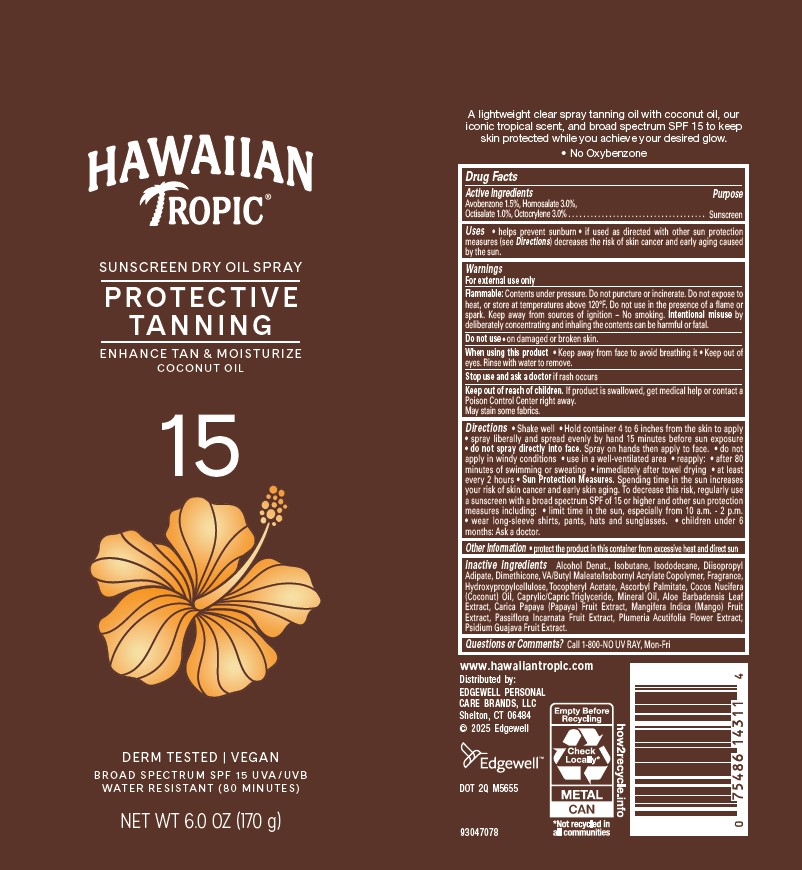 DRUG LABEL: HAWAIIAN TROPIC
NDC: 63354-302 | Form: AEROSOL, SPRAY
Manufacturer: Edgewell Personal Care Brands LLC
Category: otc | Type: HUMAN OTC DRUG LABEL
Date: 20250928

ACTIVE INGREDIENTS: AVOBENZONE 1.5 g/100 g; HOMOSALATE 3 g/100 g; OCTISALATE 1 g/100 g; OCTOCRYLENE 3 g/100 g
INACTIVE INGREDIENTS: HYDROXYPROPYL CELLULOSE, UNSPECIFIED; .ALPHA.-TOCOPHEROL ACETATE; ASCORBYL PALMITATE; COCONUT OIL; MEDIUM-CHAIN TRIGLYCERIDES; MINERAL OIL; PAPAYA; PASSIFLORA INCARNATA FRUIT; GUAVA; MANGO; ISODODECANE; PLUMERIA RUBRA FLOWER; DIMETHICONE; ALOE VERA LEAF; ALCOHOL; ISOBUTANE; DIISOPROPYL ADIPATE

Active Ingredients

Avobenzone 1.5%, Homosalate 3.0%, Octisalate 1.0%, Octocrylene 3.0%

Purpose

Sunscreen

Uses

• helps prevent sunburn • if used as directed with other sun protection measures (see Directions) decreases the risk of skin cancer and early aging caused by the sun.

Warnings

For external use only

Flammable: Contents under pressure. Do not puncture or incinerate. Do not expose to heat, or store at temperatures above 120°F. Do not use in the presence of a flame or spark. Keep away from sources of ignition – No smoking. Intentional misuse by deliberately concentrating and inhaling the contents can be harmful or fatal.

May stain some fabrics.

Do not use

• on damaged or broken skin.

When using this product

• Keep away from face to avoid breathing it • Keep out of eyes. Rinse with water to remove.

Stop use and ask a doctor

if rash occurs

Keep out of reach of children.

If product is swallowed, get medical help or contact a Poison Control Center right away.

Directions

• Shake well • Hold container 4 to 6 inches from the skin to apply • spray liberally and spread evenly by hand 15 minutes before sun exposure • do not spray directly into face. Spray on hands then apply to face. • do not apply in windy conditions • use in a well ventilated area • reapply: • after 80 minutes of swimming or sweating • immediately after towel drying • at least every 2 hours • Sun Protection Measures. Spending time in the sun increases your risk of skin cancer and early skin aging. To decrease this risk, regularly use a sunscreen with a broad spectrum SPF of 15 or higher and other sun protection measures including: • limit time in the sun, especially from 10 a.m. - 2 p.m. • wear long-sleeve shirts, pants, hats and sunglasses. • children under 6 months: Ask a doctor.

Inactive Ingredients

Alcohol Denat., Isobutane, Isododecane, Diisopropyl Adipate, Dimethicone, VA/Butyl Maleate/Isobornyl Acrylate Copolymer, Fragrance, Hydroxypropylcellulose, Tocopheryl Acetate, Ascorbyl Palmitate, Cocos Nucifera (Coconut) Oil, Caprylic/Capric Triglyceride, Mineral Oil, Aloe Barbadensis Leaf Extract, Carica Papaya (Papaya) Fruit Extract, Mangifera Indica (Mango) Fruit Extract, Passiflora Incarnata Fruit Extract, Plumeria Acutifolia Flower Extract, Psidium Guajava Fruit Extract.

Other Information

• protect the product in this container from excessive heat and direct sun

Questions or Comments?

Call 1-800-NO UV RAY, Mon-Fri

Principal Display Panel

HAWAIIAN

TROPIC

SUNSCREEN DRY OIL SPRAY

PROTECTIVE TANNING

ENHANCE TAN & MOISTURE

COCONUT OIL

15

DERM TESTED | VEGAN

BROAD SPECTRUM SPF 15 UVA / UVB

WATER RESISTANT (80 MINUTES)

NET WT 6.0 OZ (170g)